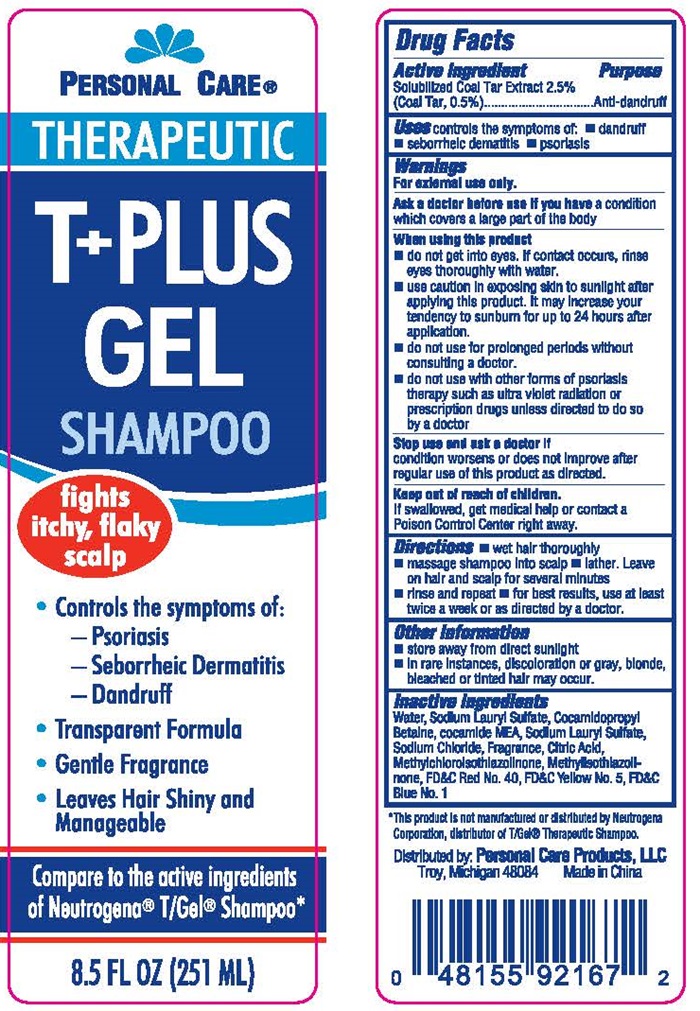 DRUG LABEL: Personal Care Therapeutic T Plus Gel
NDC: 29500-9804 | Form: SHAMPOO
Manufacturer: Personal Care Products
Category: otc | Type: HUMAN OTC DRUG LABEL
Date: 20151004

ACTIVE INGREDIENTS: COAL TAR 0.5 g/100 mL
INACTIVE INGREDIENTS: WATER; SODIUM LAURETH SULFATE; COCAMIDOPROPYL BETAINE; COCO MONOETHANOLAMIDE; SODIUM CHLORIDE; CITRIC ACID MONOHYDRATE; METHYLCHLOROISOTHIAZOLINONE; METHYLISOTHIAZOLINONE; FD&C RED NO. 40; FD&C YELLOW NO. 5; FD&C BLUE NO. 1

Drug Facts Active ingredient

Solubilized Coal Tar Extract 2.5 %

(Coal Tar, 0.5 %)

Purpose

Anti-dandruff

Keep out of reach of children.

If swallowed, get medical help or contact a Poison Control Center right away

Uses

controls the symptoms of:

- dandruff
- seborrheic dermatitis
- psoriasis

Warnings

For external use only.

Ask a doctor before use if you have

a condition which covers a large part of the body.

When using this product

- do not get into eyes. If contact occurs, rinse eyes thoroughly with water.
- use caution in exposing skin to sunlight after applying this product. It may increase your tendency to sunburn for up to 24 hours after application.
- do not use for prolonged periods without consulting a doctor.
- do not use with other forms of psoriasis therapy such as ultra violet radiation or prescription drugs unless directed to do so by a doctor.

Stop use and ask a doctor if

condition worsens or does not improve after regular use of this product as directed.

Directions

- wet hair thoroughlymassage shampoo into scalp
- lather. Leave on hair and scalp for several minutes.
- rinse and repeat
- for best results, use at least twice a week or as directed by a doctor.

Other information

- store away from direct sunlight
- in rare instances, discoloration or gray, blonde, bleached or tinted hair may occur.

Inactive ingregients

Water, Sodium Laureth Sullfate, Cocamidopropyl Betadine, cocamide MEA, Sodium Lauryl Sulfate, Sodium Chloride, Fragrance, Citric Acid, Methylchlorisothiazolinone, Methylisothiazolinone, FD&C Red No. 40, FD&C Yellow No. 5, FD&C Blue No, 1

Personal Care T+PLUS GEL SHAMPOO product label

PERSONAL CARE®

THERAPEUTIC

T + GEL

SHAMPOO

fights itchy, flaky scalp

- Controls the symptoms of:

−Psoriasis

−Seborrheic Dermatitis

−Dandruff

- Transparent Formula
- Gentle Fragrance
- Leaves Hair Shiny and Manageable

Compare to the active ingredients of Neutrogena T/Gel® Shampoo*

8.5 FL OZ (251 ML)

*This product is not manufactured or distributed by Neutrogena Corporation, distributor Of T/Gel® Therapeautic Shampoo.

Distributed by:
Personal Care Products, LLC
Troy, Michigan 48084 Made in China